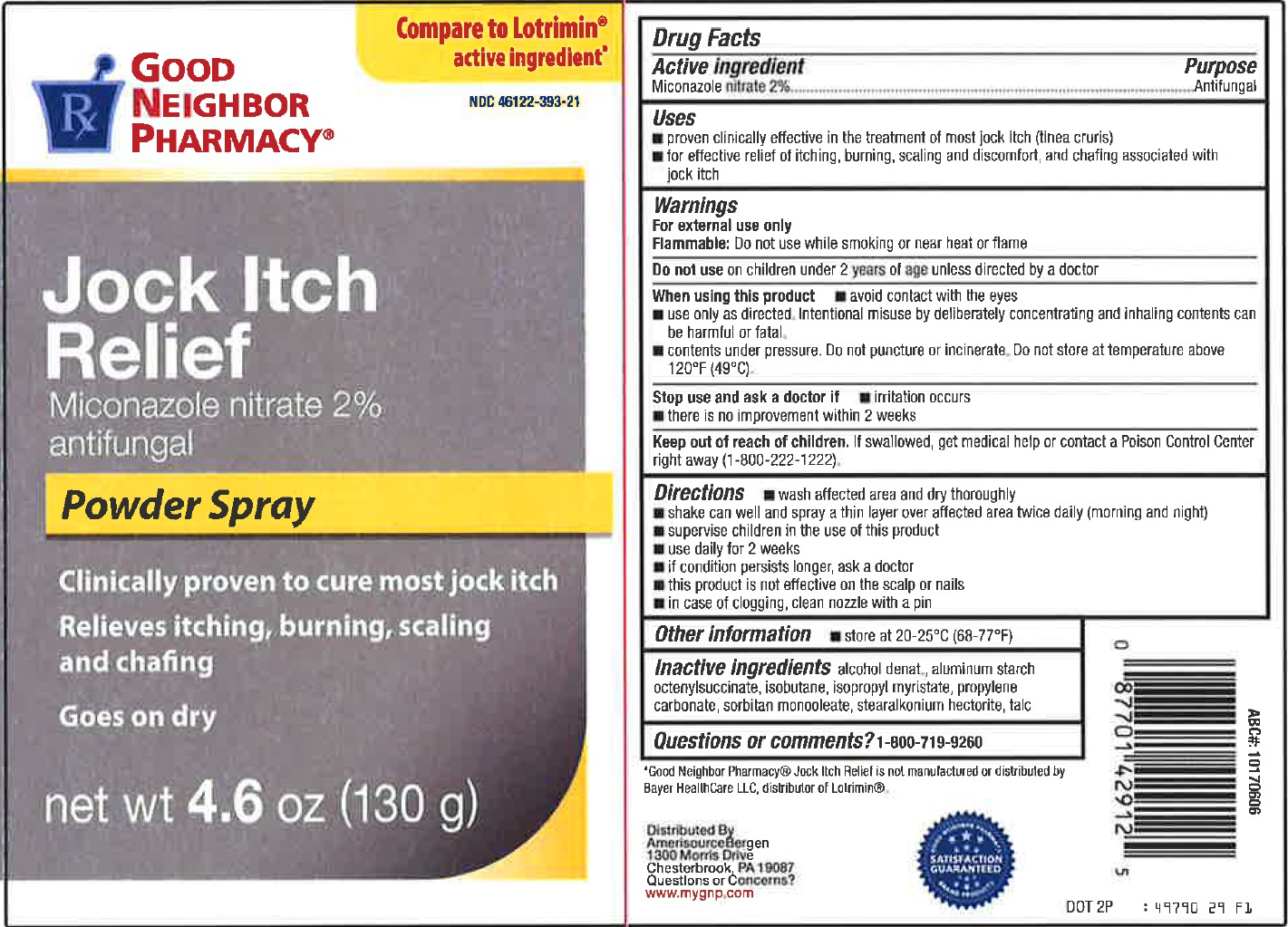 DRUG LABEL: Good Neighbor Pharmacy Jock Itch Relief Antifungal
NDC: 23667-819 | Form: SPRAY
Manufacturer: Formulated Solutions, LLC
Category: otc | Type: HUMAN OTC DRUG LABEL
Date: 20231208

ACTIVE INGREDIENTS: MICONAZOLE NITRATE 20 mg/1 g
INACTIVE INGREDIENTS: ALCOHOL; ALUMINUM STARCH OCTENYLSUCCINATE; ISOBUTANE; ISOPROPYL MYRISTATE; PROPYLENE CARBONATE; SORBITAN; STEARALKONIUM HECTORITE; TALC

Good Neighbor Pharmacy Jock Itch Relief Miconazole Nitrate Antifungal

Active ingredient

Miconazole Nitrate 2%

Purpose

Antifungal

Uses

- proven clinically effective in the treatment of most Jack itch (tinea cruis)
- for effective relief if itching, cracking, burning, scalling and discomfort, and chating associated with jock itch

Warnings

For external use only

Flammable: Do not use while smoking or near heat or flame

Do not use

on children under 2 years of age unless directed by a doctor

When using this product

- avoid contact with the eyes
- use only as directed intentional misuse by deliberately concentrating and inhaling contents can be harmful or fatal
- contents under pressure. Do nor punture or incinerate. Do not store at temperature above 120°F (49°C).

Stop use and ask a doctor if

- irritation occurs
- there is no improvement within 2 weeks

Keep out of reach of children.

If swallowed, get medical help or contact a Poison Control Center right away (1-800-222-1222).

Directions

- wash affected area and dry thoroughly
- shake can well and spray a thin layer over affected area twice daily (morning and night)
- supervise children in the use of this product
- use daily for 2 weeks
- if condition persist longer, ask a doctor
- this product is not effective on the scalp or nails
- in case of clpgging, clean nozzle with a pin

Other information

store at 20-25°C (68-77°F)

Inactive Ingredients

alcohol denat, aluminum starch octenylsuccinate, isobutane, isopropyl myristate, propylene carbonate, sorbitan monoleate, stearalkonium hectorite, talc

Questions or comments?

1-800-719-9260